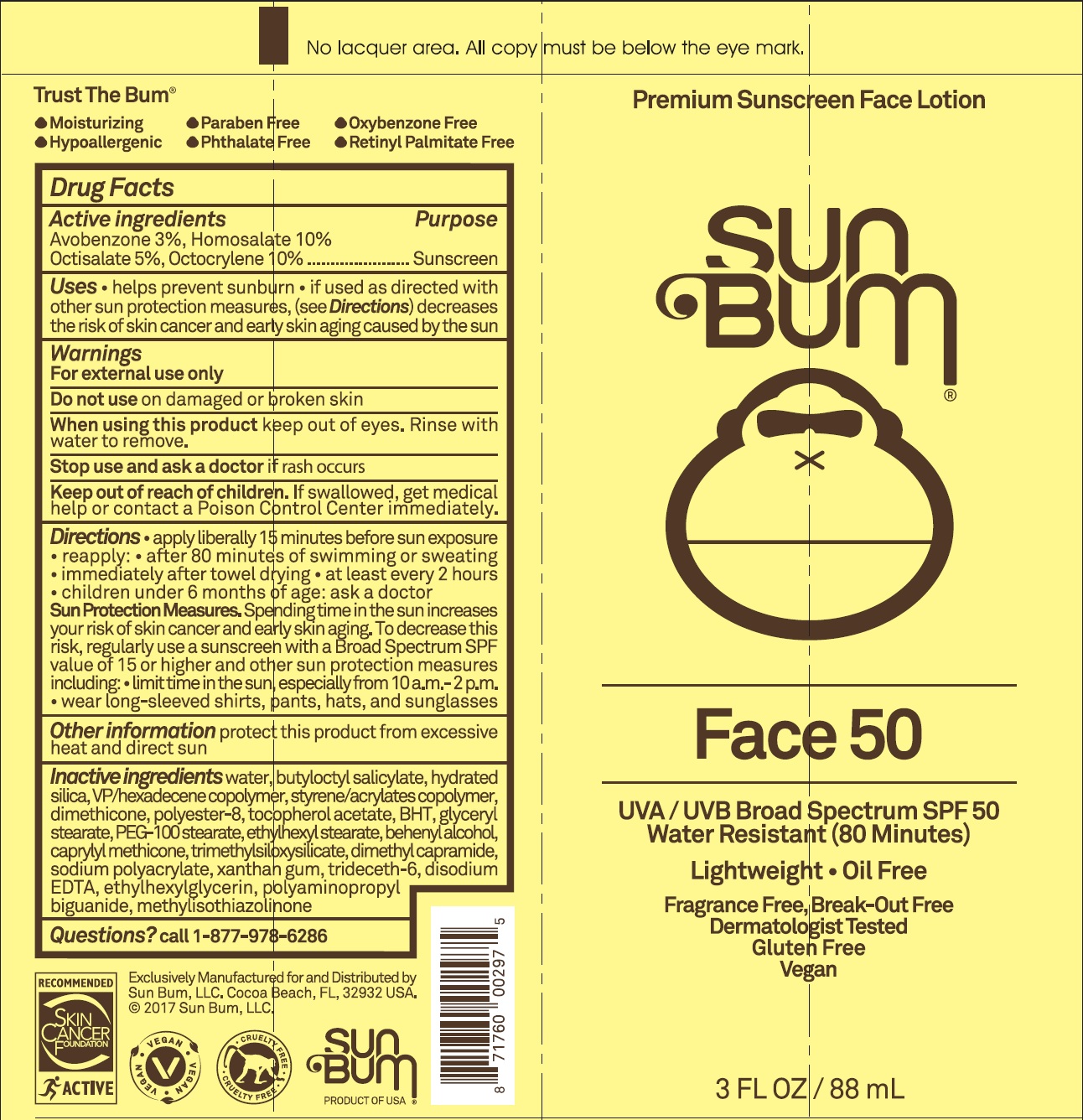 DRUG LABEL: Sun Bum Face 50 Sunscreen
NDC: 69039-250 | Form: CREAM
Manufacturer: SUN BUM, LLC
Category: otc | Type: HUMAN OTC DRUG LABEL
Date: 20220204

ACTIVE INGREDIENTS: AVOBENZONE 30 mg/1 mL; HOMOSALATE 100 mg/1 mL; OCTISALATE 50 mg/1 mL; OCTOCRYLENE 100 mg/1 mL
INACTIVE INGREDIENTS: WATER; BUTYLOCTYL SALICYLATE; HYDRATED SILICA; VINYLPYRROLIDONE/HEXADECENE COPOLYMER; DIMETHICONE; .ALPHA.-TOCOPHEROL ACETATE; BUTYLATED HYDROXYTOLUENE; GLYCERYL MONOSTEARATE; PEG-100 STEARATE; ETHYLHEXYL STEARATE; DOCOSANOL; CAPRYLYL TRISILOXANE; DIMETHYL CAPRAMIDE; XANTHAN GUM; TRIDECETH-6; EDETATE DISODIUM ANHYDROUS; ETHYLHEXYLGLYCERIN; METHYLISOTHIAZOLINONE

Sun Bum Face 50 Sunscreen Lotion

Active Ingredients

Avobenzone 3 %, Homosalate 10%

Octisalate 5.%, Octocrylene 10%

Purpose

Sunscreen

Uses

- helps prevent sunburn.
- If used as directed with other sun protection measures (see Directions), decreases the risk of skin cancer and early skin aging caused by the sun.

Warnings

For external use only.

Do not use

on damaged or broken skin.

When using this product:

Keep out of eyes. Rinse with water to remove.

Stop use and ask a doctor

if rash occurs.

Keep out of reach of children .

If swallowed, get medical help or contact a Poison Control Center immediately.

Directions

- apply liberally 15 minutes before sun exposure.
- reapply: after 80 minutes of swimming or sweating.
- immediately after towel drying.
- at least every 2 hours.
- children under 6 months of age: ask a doctor.
- Sun Protection Measures. Spending time in the sun increases your risk of skin cancer and early skin aging, To decrease this risk, regularly use a sunscreen with a Broad Spectrum SPF of 15 or higher and other sun protection measures, including:
- limit time in the sun, especially from 10 a.m. - 2 p.m.
- wear long-sleeve shirts, pants, hats, and sunglasses.

Other Information

- protect this product from excessive heat and direct sun.

Inactive Ingredients

water, butyloctyl salicylate, hydrated silica, VP/hexadecene copolymer, styrene/acrylates copolymer, dimethicone, polyester-8, tocopherol acetate, BHT, glyceryl stearate, PEG-100 stearate, ethylhexyl stearate, behenyl alcohol, caprylyl methicone, trimethylsiloxysilicate, dimethyl capramide, sodium polyacrylate, xanthan gum, trideceth-6, disodium EDTA, ethylhexylglycerin, polyaminopropyl biguanide, methylisothiazolinone

Questions or Comments?

call +1 (877) 978-6286